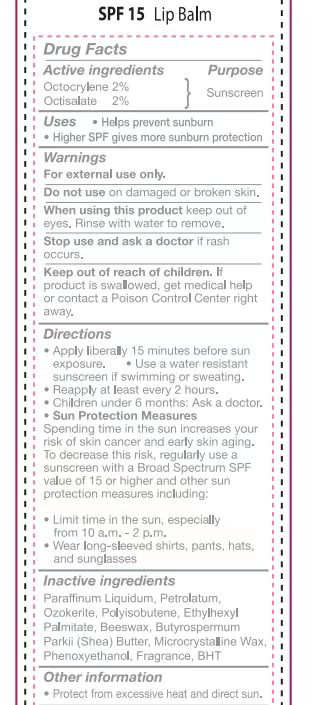 DRUG LABEL: SPF15 lip balm
NDC: 82953-009 | Form: LIPSTICK
Manufacturer: Cosmuses Cosmetics (Ningbo) Co., Ltd.
Category: otc | Type: HUMAN OTC DRUG LABEL
Date: 20241204

ACTIVE INGREDIENTS: OCTOCRYLENE 2 g/100 g; OCTISALATE 2 g/100 g
INACTIVE INGREDIENTS: POLYISOBUTYLENE (1000 MW); ETHYLHEXYL PALMITATE; MINERAL OIL; PETROLATUM; YELLOW WAX; SHEA BUTTER; MICROCRYSTALLINE WAX; PHENOXYETHANOL; BUTYLATED HYDROXYTOLUENE; CERESIN

sunscreen SPF15 scent lip balm

Active Ingredients

Octocrylene 2%

Octisalate 2%

Purpose

Sunscreen

Uses

- Helps prevent sunburn
- Higher SPF gives more sunburn protection

warnings

For external use only.

Do not use on damaged or broken skin.

When using this product keep out of eyes. Rinse with water to remove.

Stop use and ask a doctor if rash occurs.

Keep out of reach of children. If product is swallowed, get medical help or contact a Poison Control Center right away.

Directions

- Apply liberally 15 minutes before sun exposure.
- Use a water resistant sunscreen if swimming or sweating.
- Reapply at least every 2 hours
- Children under 6 months: ask a doctor
- Sun protection Measures

Spending time in the sun increases your risk of skin cancer and early skin aging. To decrease this risk, regularly use a sunscreen with a Broad Spectrum SPF value of 15 or higher and other sun protection measures including:

- Limit time in the sun, especially from 10a.m.- 2 p.m.
- Wear long-sleeved shirts, pants, hats, and sunglasses

Inactive Ingredients

Paraffinum liquidum, Petrolatum, Ozokerite, Polyisobutene, Ethylhexyl Palmitate, Beeswax, Butyrospermum Parkii (Shea) Butter, Microcrystalline Wax, Phenoxyethanol, Fragrance, BHT

Other information

Protect from excessive heat and direct sun.